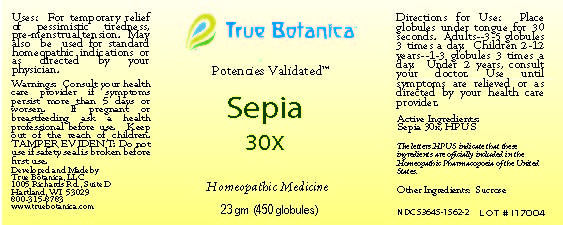 DRUG LABEL: Sepia
NDC: 53645-1562 | Form: GLOBULE
Manufacturer: True Botanica, LLC
Category: homeopathic | Type: HUMAN OTC DRUG LABEL
Date: 20230620

ACTIVE INGREDIENTS: SEPIA OFFICINALIS JUICE 30 [hp_X]/23 g
INACTIVE INGREDIENTS: SUCROSE

Sepia 30X

ACTIVE INGREDIENT

Sepia 30X, HPUS

The letters HPUS indicate that these ingredients are officially included in the Homeopathic Pharmacopoeia of the United States.

PURPOSE

For temporary relief of pessimistic tiredness, premenstrual tension. May also be used for standard homeopathic indications or as directed by your physician.

Use:

For temporary relief of pessimistic tiredness, premenstrual tension. May also be used for standard homeopathic indications or as directed by your physician.

Warnings:

Consult your health care provider if symptoms persist more than 5 days or worsen.

PREGNANCY OR BREAST FEEDING

If pregnant or breastfeeding ask a health professional before use.

Keep out of the reach of children.

DO NOT USE

TAMPER EVIDENT: Do not use if safety seal is broken before first use.

Directions for Use:

Place globules under tongue for 30 seconds. Adults~3-5 globules 3 times a day. Children 2-12 years ~ 1-3 globules 3 times a day. Under 2 years, consult your doctor. Use until symptoms are relieved or as directed by your health care provider.

Other Ingredients:

Sucrose

QUESTIONS

Developed and Made by

True Botanica, LLC

1005 Richards Rd., Suite D

Hartland, WI 53029

800-315-8783

www.truebotanica.com